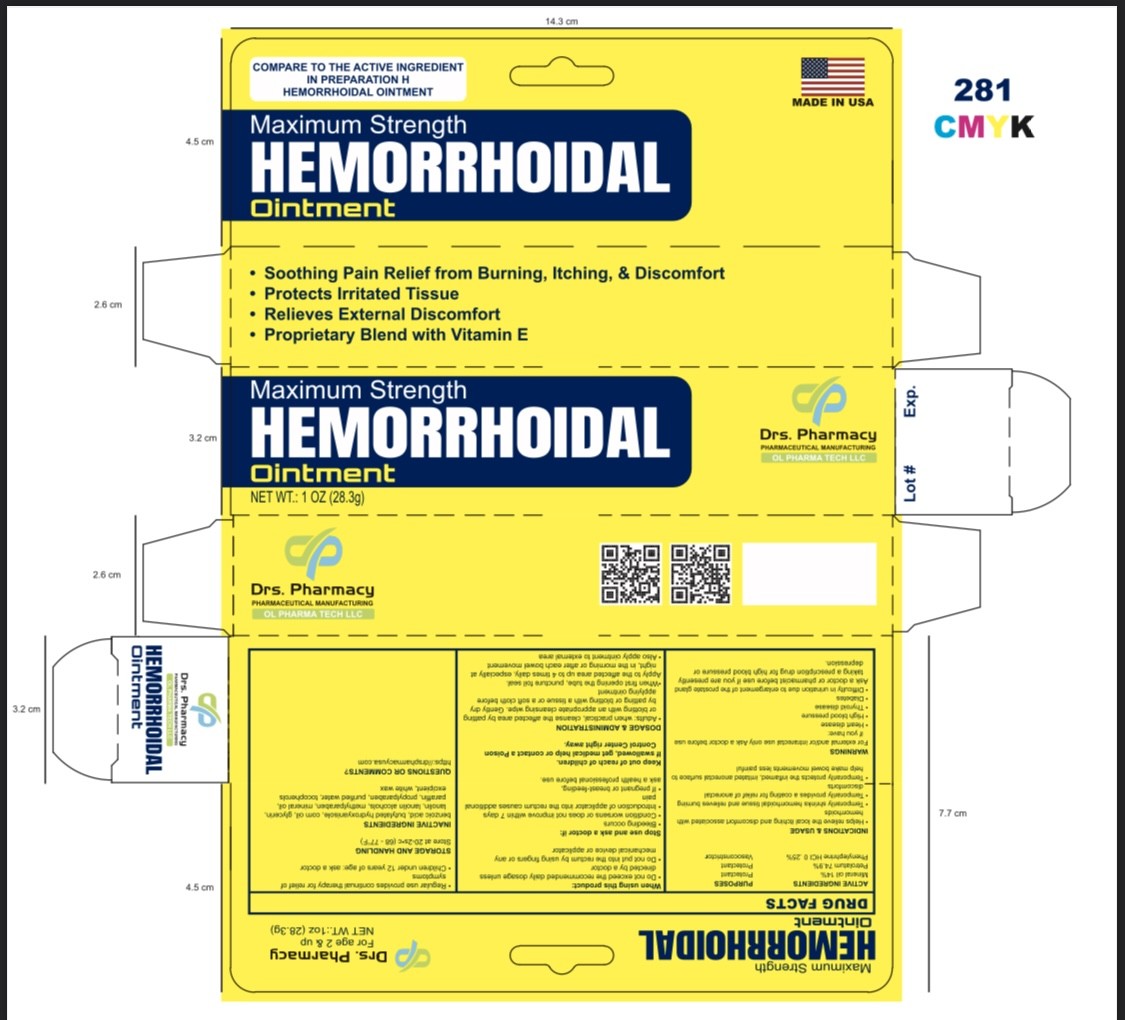 DRUG LABEL: Drs pharmacy  HEMORRHOIDAL
NDC: 80489-956 | Form: OINTMENT
Manufacturer: OL PHARMA TECH, LLC Drs PHARMACY
Category: otc | Type: HUMAN OTC DRUG LABEL
Date: 20240416

ACTIVE INGREDIENTS: PETROLATUM 749 mg/1 g; PHENYLEPHRINE HYDROCHLORIDE 2.5 mg/1 g; MINERAL OIL 140 mg/1 g
INACTIVE INGREDIENTS: BENZOIC ACID; PARAFFIN; CORN OIL; GLYCERIN; THYME; WHITE WAX; TOCOPHEROL; BUTYLATED HYDROXYANISOLE; LANOLIN ALCOHOLS; WATER; LANOLIN; METHYLPARABEN; PROPYLPARABEN

ACTIVE INGREDIENTS

1. Phenylephrine HCI, 0.25%
2. Petrolatum 74.9 %
3. mineral oil 14 %

PURPOSE

- Vasoconstrictor
- protectant

USES

- helps relieve the local itching and discomfort associated with hemorrhoids
- temporarily shrinks hemorrhoidal tissue and relieves burning
- temporarily provides a coating for relief of anorectal discomforts
- aids in protecting irritated anorectal areas
- temporarily protects the inflamed, irritated anorectal surface to help make bowel movements less painful

WARNINGS

For external use only and / or intrarectal use only

ASK A DOCTOR BEFORE USE IF YOU HAVE

- heart disease
- high blood pressure
- thyroid disease
- diabetes
- difficulty in urination due to enlargement of the prostate gland

Ask a doctor or pharmacist before use if you are

presently taking a prescription drug for high blood pressure or depression

WHEN USING THIS PRODUCT

- do not exceed the recommended daily dosage unless directed by a doctor
- do not put this product into the rectum by using fingers or any mechanical device or applicator

STOP USING AND ASK YOUR DOCTOR IF

- bleeding occurs
- condition worsens or does not improve within 7 days

IF PREGNENT OR BREAST-FEEDING

ask a health professional before use.

KEEP OUT OF REACH OF CHILDREN

If swallowed, get medical help or contact a Poison Control Center right away.

DIRECTIONS

- adults: when practical, cleanse the affected area by patting or blotting with an appropriate cleansing wipe. Gently dry by patting or blotting with a tissue or a soft cloth before applying gel.
- when first opening the tube, puncture foil seal with top end of cap
- apply externally to the affected area up to 4 times daily, especially at night, in the morning or after each bowel movement
- children under 12 years of age: ask a doctor

OTHER INFORMATION

store at 20-25°C (68-77°F)

INACTIVE INGREDIENTS

methylparaben, propylparaben, purified water, benzoic acid, butylated hydroxyanisole, corn oil, glycerine, lanolin, lanolin alcohols, mineral oil, paraffin, tocopherol, white wax

QUESTIONS

www.drspharmacyusa.com